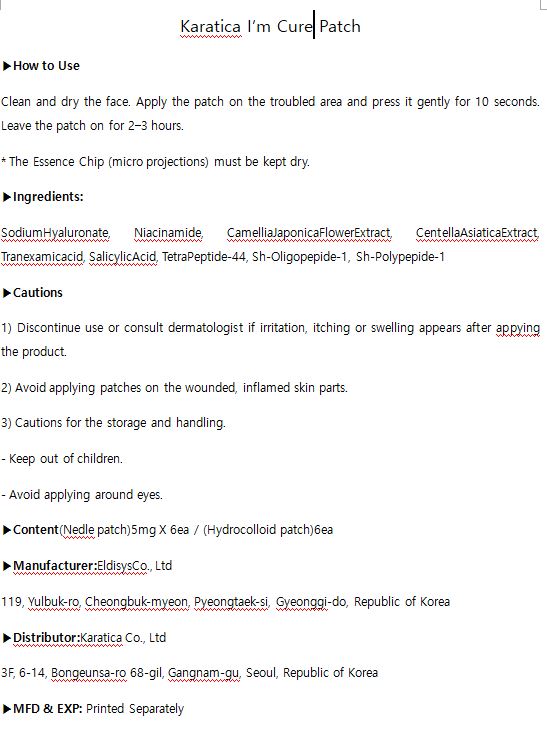 DRUG LABEL: KARATICA I M CURE
NDC: 70514-0012 | Form: PATCH
Manufacturer: Karatica Co., Ltd
Category: otc | Type: HUMAN OTC DRUG LABEL
Date: 20181204

ACTIVE INGREDIENTS: NIACINAMIDE 2.7 mg/100 mg
INACTIVE INGREDIENTS: HYALURONATE SODIUM; WATER

ACTIVE INGREDIENT

niacinamide

INACTIVE INGREDIENT

SodiumHyaluronate, Niacinamide, CamelliaJaponicaFlowerExtract, CentellaAsiaticaExtract, Tranexamicacid, SalicylicAcid, TetraPeptide-44, Sh-Oligopepide-1, Sh-Polypepide-1

PURPOSE

skin soothing and care

keep out or reach of the children

INDICATIONS AND USAGE

Clean and dry the face. Apply the patch on the troubled area and press it gently for 10 seconds. Leave the patch on for 2‒3 hours.

* The Essence Chip (micro projections) must be kept dry.

WARNINGS

1) Discontinue use or consult dermatologist if irritation, itching or swelling appears after appying the product.

2) Avoid applying patches on the wounded, inflamed skin parts.

3) Cautions for the storage and handling.

- Keep out of children.

- Avoid applying around eyes.

DOSAGE AND ADMINISTRATION

for external use only